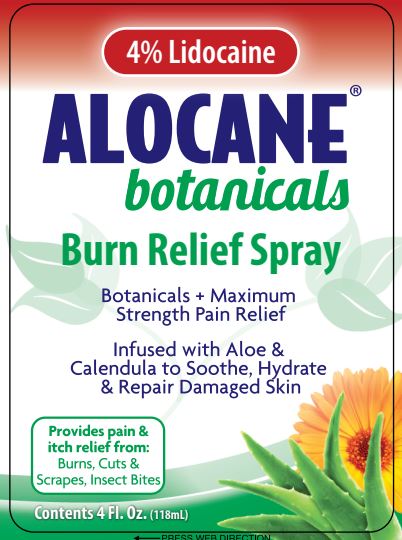 DRUG LABEL: Alocane Botanicals
NDC: 68229-405 | Form: SPRAY
Manufacturer: Quest Products, LLC.
Category: otc | Type: HUMAN OTC DRUG LABEL
Date: 20241105

ACTIVE INGREDIENTS: LIDOCAINE HYDROCHLORIDE 4 g/100 mL
INACTIVE INGREDIENTS: MANNITOL; SODIUM HYDROXIDE; DEXPANTHENOL; LIMOSILACTOBACILLUS FERMENTUM; HYALURONATE SODIUM; GLYCERIN; ECHINACEA PURPUREA ROOT; ALOE VERA LEAF; HYDROXYETHYL CELLULOSE (5500 MPA.S AT 2%); PHENOXYETHANOL; WATER; CALENDULA OFFICINALIS FLOWER

Alocane® Botanicals

Drug Facts

Active Ingredient

Lidocaine HCL 4%

Purpose

Topical Pain Relief

Uses

For the temporary relief of pain and itching associated with:

- Sunburn
- Minor Skin Irritation
- Minor Burns
- Minor Cuts & Scrapes
- Insect Bites

Warnings

For external use only. Avoid contact with eyes.

Do not use:

- in large quantities, or over large areas of the body
- Over raw surfaces or blistered areas
- If you have an allergy to any of the ingredients

Ask a doctor before use if you have a severe burn or deep cut, broken or compromised skin

Stop use and ask doctor:

- if condition worsens
- if symptoms persist for more than 7 days or clear up and occur again within a few days.

Keep out of reach of children. If swallowed, get medical help or contact a Poison Control Center right away.

PREGNANCY OR BREAST FEEDING

If pregnant or breast-feeding, ask a health care professional before use.

Directions:

Adults and Children 2 years of age or older:

Shake well. Apply top affected area not more than 3-4 times daily. To apply to face, spray on palm and carefully apply.

Children under 2 years of age, ask a doctor before use.

Other Information

Store at 15-30°C (59-86°F)

Inactive Ingredients

Water, Phenoxyethanol, Aloe Vera Leaf Juice, Lactobacilus Ferment, Echinacea Purpurea Root Extract, Calendula Officinalis Flower Extract, Sodium Hyaluronate, D-Panthenol, Glycerin, Hydroxyethyl Cellulose, Mannitol, Sodium Hydroxide